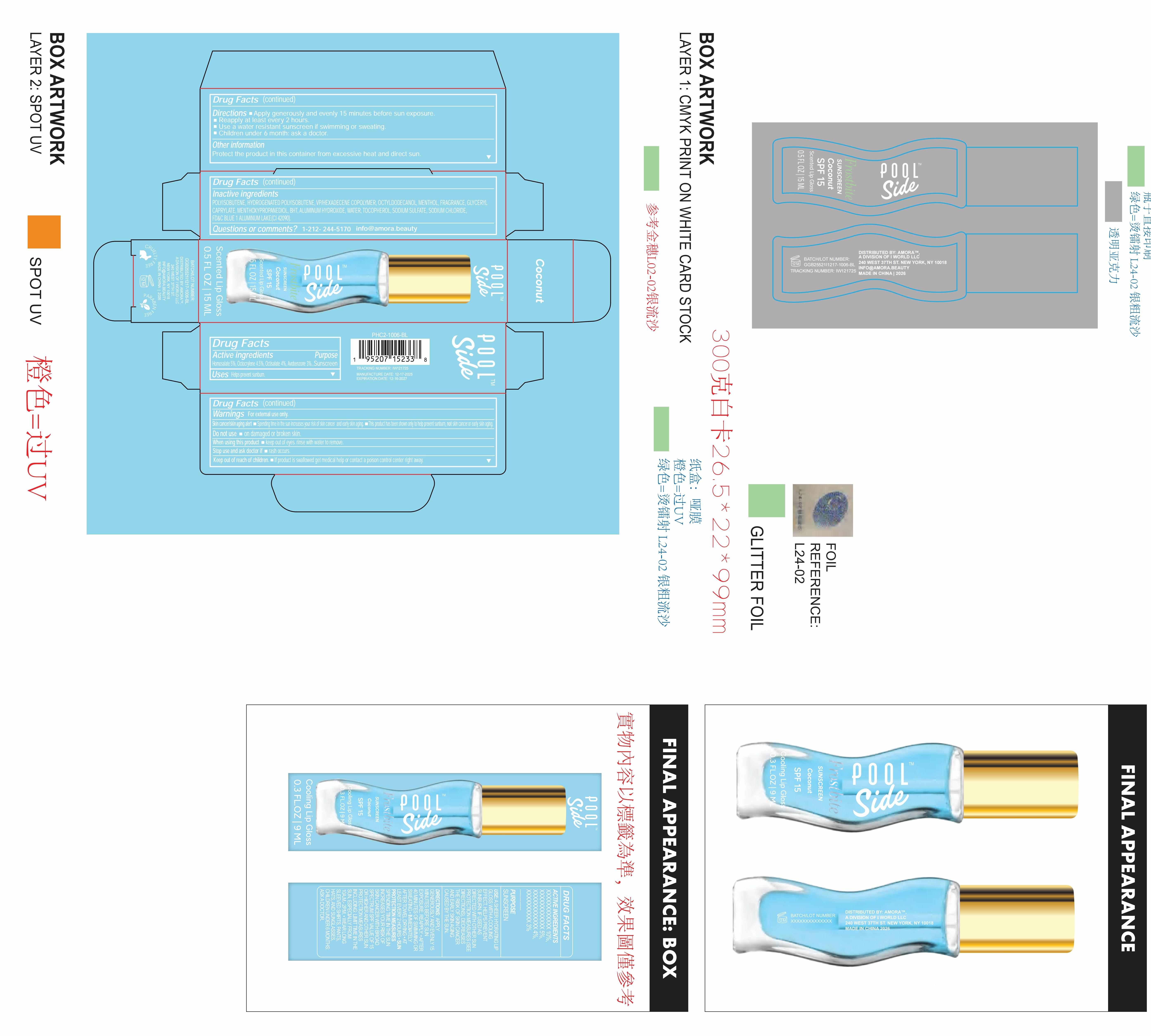 DRUG LABEL: Poolside Frostbite Sunscreen coconut SPF 15 Scented lip gloss
NDC: 85161-158 | Form: LIQUID
Manufacturer: Longway Technology(Guangzhou)Co.,Ltd.
Category: otc | Type: HUMAN OTC DRUG LABEL
Date: 20251204

ACTIVE INGREDIENTS: OCTOCRYLENE 0.045 g/1 mL; AVOBENZONE 0.03 g/1 mL; HOMOSALATE 0.05 g/1 mL; OCTISALATE 0.04 g/1 mL
INACTIVE INGREDIENTS: ALUMINUM HYDROXIDE; HYDROGENATED POLYISOBUTENE (450 MW); POLYISOBUTYLENE (1300 MW); WATER; MENTHOL; FRAGRANCE 13576; OCTYLDODECANOL; VP/HEXADECENE COPOLYMER; MENTHOXYPROPANEDIOL; SODIUM CHLORIDE; CI 42090; BHT; TOCOPHEROL; SODIUM SULFATE; GLYCERYL CAPRYLATE

ACTIVE INGREDIENT

Homosalate 5%, Octocrylene 4.5%, Octisalate 4%, Avobenzone 3%

INACTIVE INGREDIENT

POLYISOBUTENE, HYDROGENATED POLYISOBUTENE, VP/HEXADECENE COPOLYMER, OCTYLDODECANOL, MENTHOL, FRAGRANCE, GLYCERYL CAPRYLATE, MENTHOXYPROPANEDIOL, BHT, ALUMINUM HYDROXIDE, WATER, TOCOPHEROL, SODIUM SULFATE, SODIUM CHLORIDE,FD&C BLUE 1 ALUMINUM LAKE(CI 42090).

KEEP OUT OF REACH OF CHILDREN

If product is swallowed get medical help or contact a poison control center right away.

PURPOSE

Sunscreen

QUESTIONS

1-212- 244-5170info@amora.beauty

OTHER SAFETY INFORMATION

Protect the product in this container from excessive heat and direct sun.

DOSAGE AND ADMINISTRATION

Apply generously and evenly 15 minutes before sun exposure.
Reapply at least every 2 hours.
Use a water resistant sunscreen if swimming or sweating.
Children under 6 month: ask a doctor.

WARNINGS

For external use only.

Skin cancer/skin aging alert Spending time in the sun increases your risk of skin cancer and early skin aging. This product has been shown only to help prevent sunburn, not skin cancer or early skin aging.

Do not use on damaged or broken skin
When using this product keep out of eyes. rinse with water to remove.

Stop use and ask doctor if rash occurs.

Keep out of reach of children. If product is swallowed get medical help or contact a poison control center right away

INDICATIONS AND USAGE

Helps prevent sunburn.